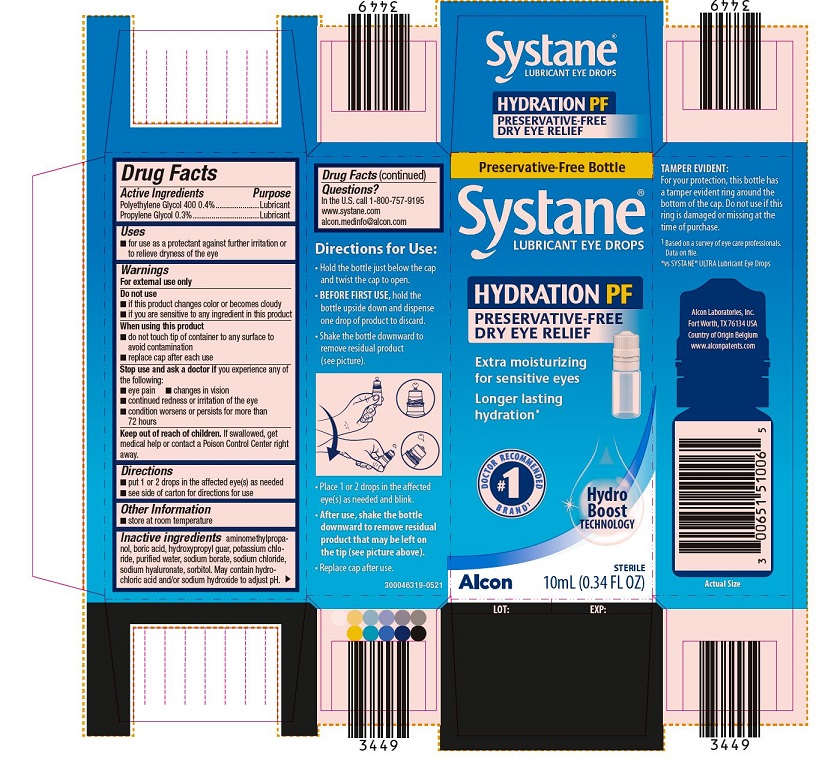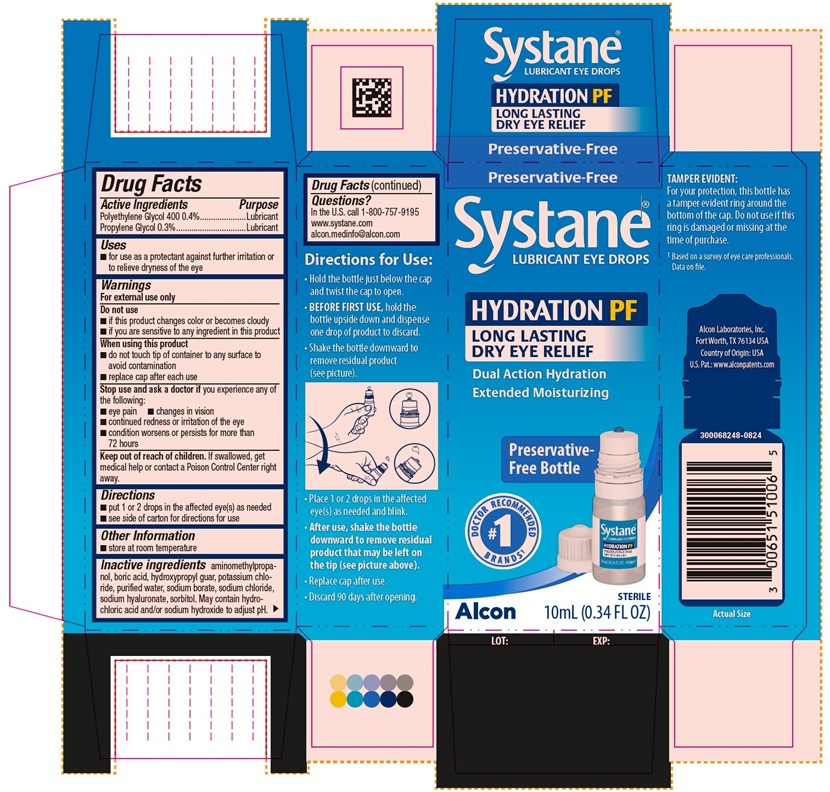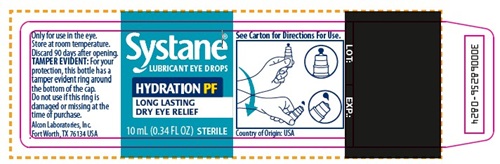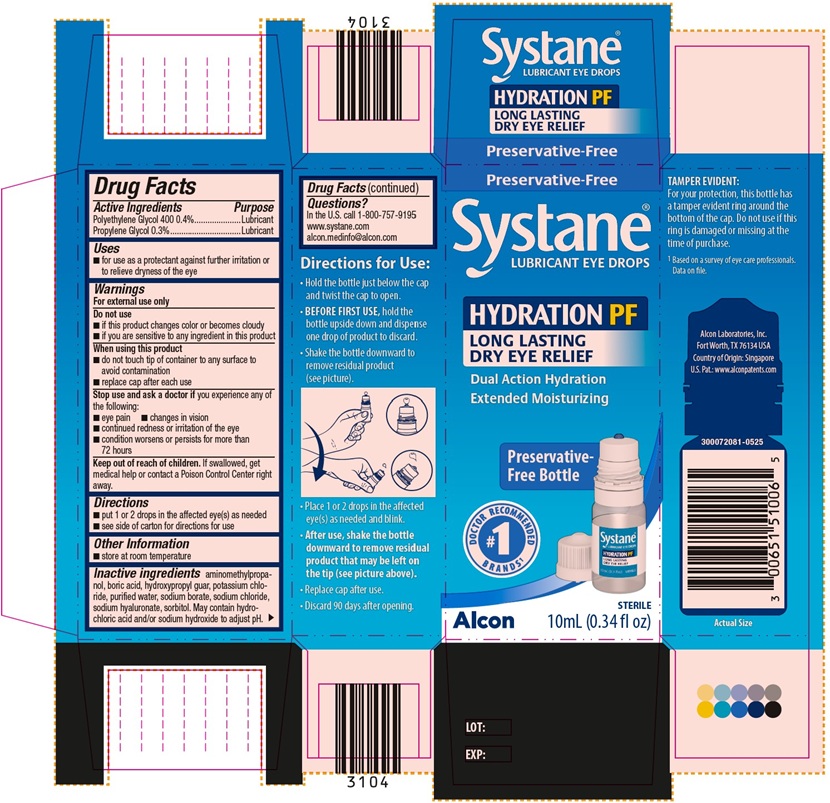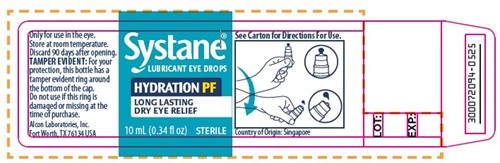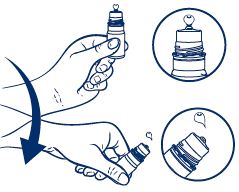 DRUG LABEL: SYSTANE HYDRATION PF PRESERVATIVE FREE
NDC: 0065-1510 | Form: SOLUTION/ DROPS
Manufacturer: Alcon Laboratories, Inc.
Category: otc | Type: HUMAN OTC DRUG LABEL
Date: 20250723

ACTIVE INGREDIENTS: Polyethylene Glycol 400 4 mg/1 mL; Propylene Glycol 3 mg/1 mL
INACTIVE INGREDIENTS: Aminomethylpropanol; Boric Acid; Guaraprolose (3500 Mpa.S At 1%); Potassium Chloride; Water; Sodium Borate; Sodium Chloride; Hyaluronate Sodium; Hydrochloric Acid; Sodium Hydroxide; Sorbitol

Drug Facts

ACTIVE INGREDIENT

Active Ingredients | Purpose
Polyethylene Glycol 400 0.4% | Lubricant
Propylene Glycol 0.3% | Lubricant

Uses

- for use as a protectant against further irritation or to relieve dryness of the eye

Warnings

For external use only

Do not use

- if this product changes color or becomes cloudy
- if you are sensitive to any ingredient in this product

When using this product

- do not touch tip of container to any surface to avoid contamination
- replace cap after each use

Stop use and ask a doctor if you experience any of the following:

- eye pain
- changes in vision
- continued redness or irritation of the eye
- condition worsens or persists for more than 72 hours

Keep out of reach of children.

If swallowed, get medical help or contact a Poison Control Center right away.

Directions

- put 1 or 2 drops in the affected eye(s) as needed.
- see side of carton for directions for use

Other information

- store at room temperature

Inactive ingredients

aminomethylpropanol, boric acid, hydroxypropyl guar, potassium chloride, purified water, sodium borate, sodium chloride, sodium hyaluronate, sorbitol. May contain hydrochloric acid and/or sodium hydroxide to adjust pH.

Questions?

In the U.S. call 1 (800) 757-9195
www.systane.com
alcon.medinfo@alcon.com

Directions for Use:

- Hold the bottle just below the cap and twist the cap to open.
- BEFORE FIRST USE, hold the bottle upside down and dispense one drop of product to discard.
- Shake the bottle downward to remove residual product (see picture).

- Place 1 or 2 drops in the affected eye(s) as needed and blink.
- After use, shake the bottle downward to remove residual product that may be left on the tip (see picture above).
- Replace cap after use.
- Discard 90 days after opening.

PRINCIPAL DISPLAY PANEL

Preservative-Free
SYSTANE®
Lubricant Eye Drops
HYDRATION PF
LONG LASTING
DRY EYE RELIEF
Dual Action Hydration
Extended Moisturizing
Preservative-Free Bottle
#1 Doctor Recommended Brands^1
Alcon
STERILE 10 mL (0.34 FL OZ)
Side Panel
TAMPER EVIDENT:
For your protection, this bottle has a tamper evident ring around the bottom of the cap. Do not use if this ring is damaged or missing at the time of purchase.
^1Based on a survey of eye care professionals. Data on file.
Alcon Laboratories, Inc.
Fort Worth, TX 76134 USA
Country of Origin: USA
U.S. Pat: www.alconpatents.com
300068248-0824

Preservative-Free Bottle
SYSTANE®
Lubricant Eye Drops
HYDRATION PF
PRESERVATIVE-FREE
DRY EYE RELIEF
Extra moisturizing for sensitive eyes
Longer lasting hydration*
#1 Doctor Recommended Brand^1
Hydro Boost Technology
Alcon
STERILE 10 mL (0.34 FL OZ)
Side Panel
TAMPER EVIDENT:
For your protection, this bottle has a tamper evident ring around the bottom of the cap. Do not use if this ring is damaged or missing at the time of purchase.
^1Based on a survey of eye care professionals. Data on file.
*vs SYSTANE® ULTRA Lubricant Eye Drops
Alcon Laboratories, Inc.
Fort Worth, TX 76134 USA
Country of Origin Belgium
www.alconpatents.com
300046319-0521

Preservative-Free
SYSTANE®
Lubricant Eye Drops
HYDRATION PF
LONG LASTING
DRY EYE RELIEF
Dual Action Hydration
Extended Moisturizing
Preservative-Free Bottle
#1 Doctor Recommended Brands^1
Alcon
STERILE 10 mL (0.34 fl oz)
Side Panel
TAMPER EVIDENT:
For your protection, this bottle has a tamper evident ring around the bottom of the cap. Do not use if this ring is damaged or missing at the time of purchase.
^1 Based on a survey of eye care professionals. Data on file.
Alcon Laboratories, Inc.
Fort Worth, TX 76134 USA
Country of Origin: Singapore
U.S. Pat.: www.alconpatents.com
300072081-0525

SYSTANE®
Lubricant Eye Drops
HYDRATION PF
LONG LASTING
DRY EYE RELIEF
STERILE
10mL (0.34 FL OZ)
Only for use in the eye.
Store at room temperature.
Discard 90 days after opening.
TAMPER EVIDENT: For your protection, this bottle has a tamper evident ring around the bottom of the cap. Do not use if this ring is damaged or missing at the time of purchase.
Alcon Laboratories, Inc.
Fort Worth, TX 76134 USA
See Carton for Directions For Use.

Country of Origin: USA
LOT: EXP:
300068256-0824

SYSTANE®
Lubricant Eye Drops
HYDRATION PF
LONG LASTING
DRY EYE RELIEF
STERILE
10mL (0.34 fl oz)
Only for use in the eye.
Store at room temperature.
Discard 90 days after opening.
TAMPER EVIDENT: For your protection, this bottle has a tamper evident ring around the bottom of the cap. Do not use if this ring is damaged or missing at the time of purchase.
Alcon Laboratories, Inc.
Fort Worth, TX 76134 USA
See Carton for Directions For Use.
Country of Origin: Singapore
LOT: EXP:
300072094-0525